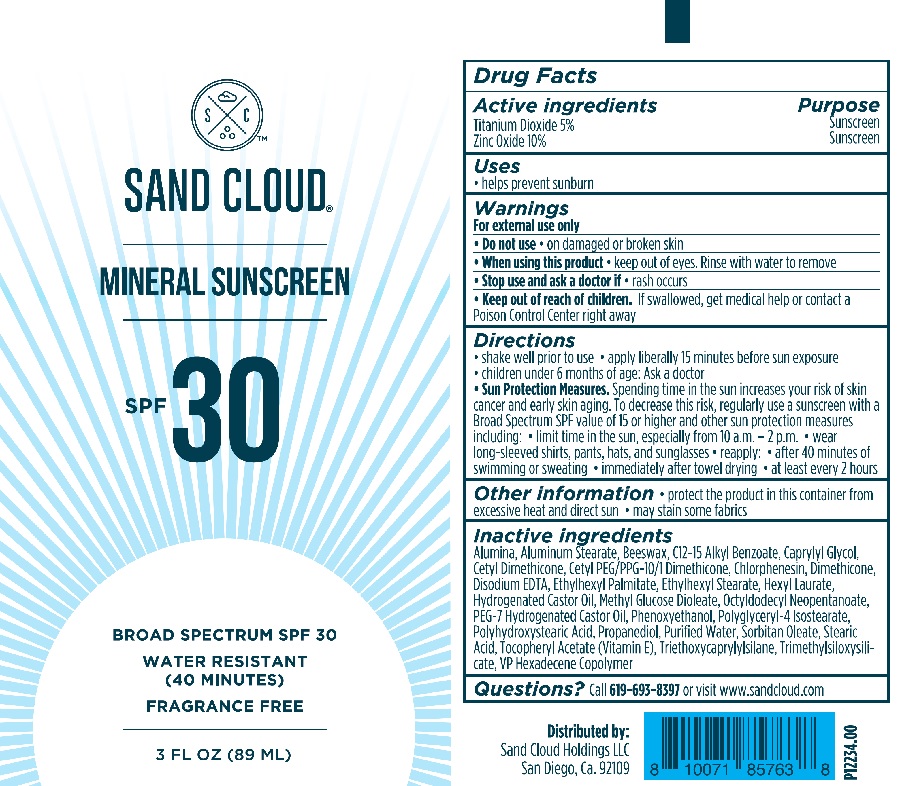 DRUG LABEL: Sand Cloud Mineral Sunscreen
NDC: 83081-2045 | Form: LOTION
Manufacturer: Sand Cloud Holdings, LLC
Category: otc | Type: HUMAN OTC DRUG LABEL
Date: 20251219

ACTIVE INGREDIENTS: TITANIUM DIOXIDE 54 mg/1 mL; ZINC OXIDE 108 mg/1 mL
INACTIVE INGREDIENTS: ETHYLHEXYL PALMITATE; ETHYLHEXYL STEARATE; CAPRYLYL GLYCOL; HEXYL LAURATE; HYDROGENATED CASTOR OIL; METHYL GLUCOSE DIOLEATE; CHLORPHENESIN; OCTYLDODECYL NEOPENTANOATE; PEG-7 HYDROGENATED CASTOR OIL; POLYGLYCERYL-4 ISOSTEARATE; PHENOXYETHANOL; PROPANEDIOL; WATER; SORBITAN MONOOLEATE; STEARIC ACID; .ALPHA.-TOCOPHEROL ACETATE; HEXADECYL POVIDONE (4 HEXADECYL BRANCHES/REPEAT); DIMETHICONE; TRIMETHYLSILOXYSILICATE (M/Q 0.8-1.0); CETYL DIMETHICONE 25; POLYHYDROXYSTEARIC ACID (2300 MW); ALUMINUM STEARATE; TRIETHOXYCAPRYLYLSILANE; ALUMINUM OXIDE; YELLOW WAX; ALKYL (C12-15) BENZOATE; CETYL PEG/PPG-10/1 DIMETHICONE (HLB 5); EDETATE DISODIUM

Sand Cloud Mineral Sunscreen

Active ingredients

Titanium Dioxide 5%

Zinc Oxide 10%

Purpose

Sunscreen

Uses

- helps prevent sunburn

Warnings

For external use only

Do not use

- on damaged or broken skin

When using this product

- keep out of eyes. Rinse with water to remove

Stop use and ask a doctor if

- rash occurs

Keep out of reach of children.

If swallowed, get medical help or contact a Poison Control Center right away

Directions

- shake well prior to use
- apply liberally 15 minutes before sun exposure
- children under 6 months of age: ask a doctor
- Sun Protection Measures. Spending time in the sun increases your risk of skin cancer and early skin aging. To decrease this risk, regularly use a sunscreen with a Broad Spectrum SPF value of 15 or higher and other sun protection measures including:
- limit time in the sun especially from 10 a.m.- 2 p.m.
- wear long-sleeved shirts, pants, hats, and sunglasses
- reapply :
- after 40 minutes of swimming or sweating
- immediately after towel drying
- at least every 2 hours

Other information

- protect the product in this container from excessive heat and direct sun
- may stain some fabrics

Inactive ingredients

Alumina, Aluminum Stearate, Beeswax, C12-15 Alkyl Benzoate, Caprylyl Glycol, Cetyl Dimethicone, Cetyl PEG/PPG-10/1 Dimethicone, Chlorphenesin, Dimethicone, Disodium EDTA, Ethylhexyl Palmitate, Ethylhexyl Stearate, Hexyl Laurate, Hydrogenated Castor Oil, Methyl Glucose Dioleate, Octyldodecyl Neopentanoate, PEG-7 Hydrogenated Castor Oil, Phenoxyethanol, Polyglyceryl-4 Isostearate, Polyhydroxystearic Acid, Propanediol, Purified Water, Sorbitan Oleate, Stearic Acid, Tocopheryl Acetate (Vitamin E), Triethoxycaprylylsilane, Trimethylsiloxysilicate, VP Hexadecene Copolymer

Questions?

Call 619-693-8397 or visit www.sandcloud.com

Sand Cloud Mineral Sunscreen 3oz

SAND CLOUD

MINERAL SUNSCREEN

SPF 30

BROAD SPECTRUM SPF 30

WATER RESISTANT

(40 MINUTES)

FRAGRANCE FREE

P12234.00